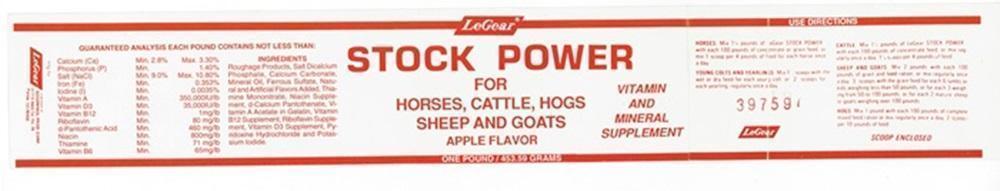 DRUG LABEL: LeGear STOCK
NDC: 42822-203 | Form: POWDER
Manufacturer: LeGear Animal Health
Category: animal | Type: OTC ANIMAL DRUG LABEL
Date: 20211101

ACTIVE INGREDIENTS: CYANOCOBALAMIN 1 mg/453.59 g; RIBOFLAVIN 80 mg/453.59 g; PANTOTHENIC ACID 460 mg/453.59 g; NIACIN 800 mg/453.59 g; THIAMINE MONONITRATE 71 mg/453.59 g; PYRIDOXINE 65 mg/453.59 g
INACTIVE INGREDIENTS: CALCIUM CARBONATE; CALCIUM PHOSPHATE, DIBASIC, ANHYDROUS; MINERAL OIL; FERROUS SULFATE; CALCIUM PANTOTHENATE; CHOLECALCIFEROL; PYRIDOXINE HYDROCHLORIDE; POTASSIUM IODIDE; VITAMIN A ACETATE

USE

VITAMIN AND MINERAL SUPPLEMENT

DIRECTIONS

HORSES: Mix 1 1/4 pounds of LeGear STOCK POWDER with each 100 pounds of concentrate or grain feed, or mix 1 scoop per 4 pounds of feed for each horse once a day.

YOUNG COLTS AND YEARLINGS: Mix 1 1/2 scoops with the wet or dry feed for each young colt, or 2 scoops for each yearling, regularly once a day.

CATTLE: Mix 1 1/2 pounds of LeGear STOCK POWDER with each 100 pounds of concentrate feed , or mix regularly once a day 1 1/4 scoops per 4 pounds of feed.

SHEEP AND GOATS: Mix 2 pounds with each 100 pounds of grain and feed ration, or mix regularly once a day 3 scoops with the grain feed for each 6 lambs or kids weighing less than 50 pounds, or for each 3 weighing from 50 to 100 pounds, or for each 2 mature sheep or goats weighing over 100 pounds.

HOGS: Mix 1 pound with each 100 pounds of complete mixed feed ration or mix regularly once a day, 2 scoops per 10 pounds of feed

SCOOP ENCLOSED

INGREDIENTS

GUARANTEED ANALYSIS EACH POUND CONTAINS NOT LESS THAN:

Calcium (Ca) Min. 2.8% Max. 3.30%

Phosphorus Min. 1.40%

Salt (NaCl) Min. 9.0% Max. 10.80%

Iron (Fe) Min. 0.353%

Iodine (I) Min. 0.0035%

Vitamin A Min. 350,000IU/lb

Vitamin D3 Min. 35,000IU/lb

Vitamin B12 Min. 1 mg/lb

Riboflavin Min. 80 mg/lb

d-Pantothenic Acid Min. 460 mg/lb

Niacin Min. 800 mg/lb

Thiamine Min. 71 mg/lb

Vitamin B6 Min. 65 mg/lb

INGREDIENTS

Roughage Products, Salt Dicalcium Phosphate, Calcium Carbonate, Mineral Oil, Ferrous Sulfate, Natural and Artificial Flavors Added, Thiamine Mononitrate, Niacin Supplement, d-Calcium Pantothenate, Vitamin A Acetate in Gelatin, Vitamin B12 Supplement, Riboflavin Supplement, Vitamin D3 Supplement, Pyridoxine Hydrochloride and Potassium Iodide.

LeGear STOCK POWDER Product Label

LeGear

STOCK POWDER

FOR
HORSES, CATTLE, HOGS
SHEEP AND GOATS

APPLE FLAVOR

VITAMIN AND MINERAL SUPPLEMENT

ONE POUND/ 453.59 GRAMS

mfg for

LeGear

a division of

GOODWINOL PROD. CORP.4 1710 Weld. Co. Rd. 29

Pierce, CO 80650

res